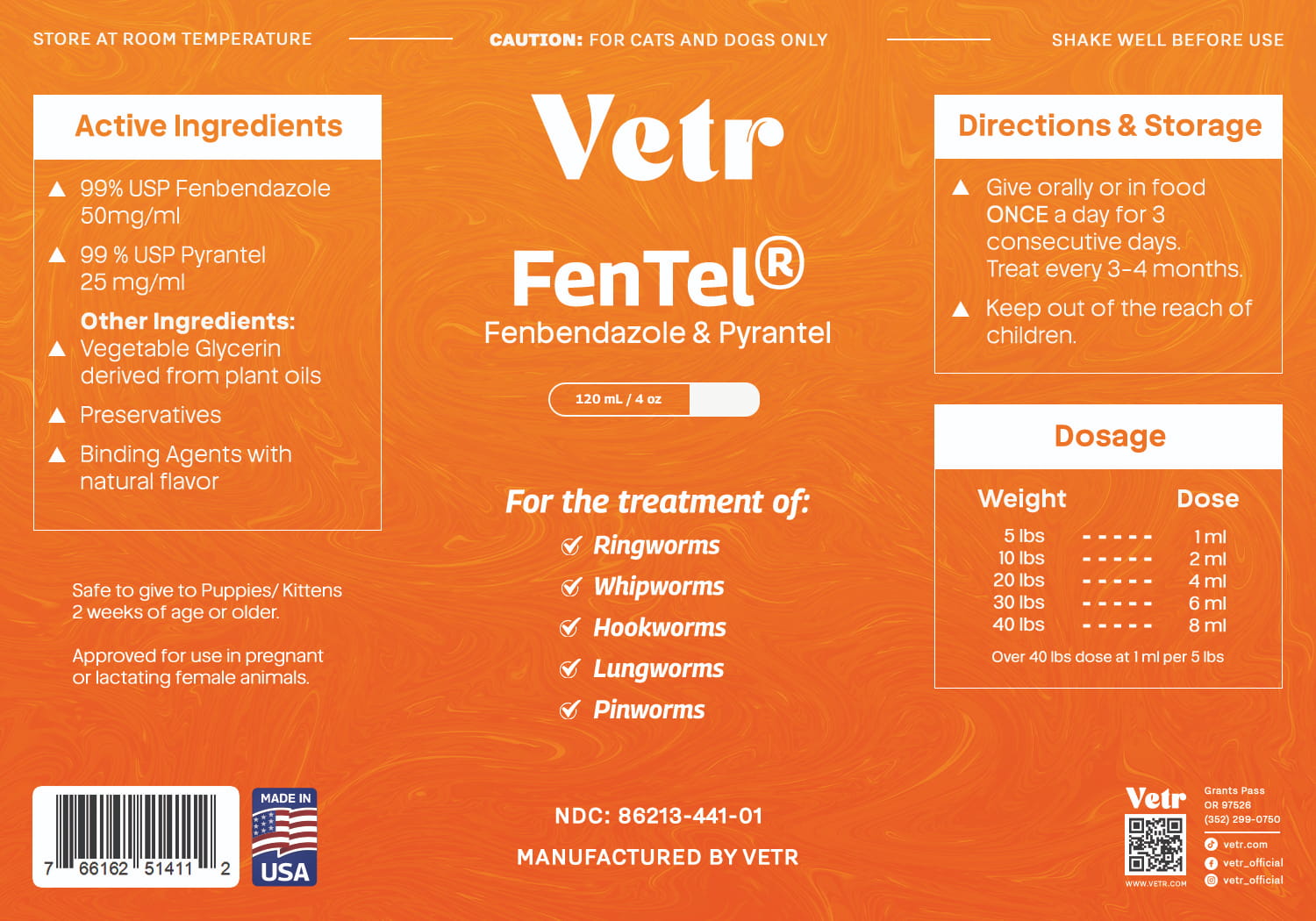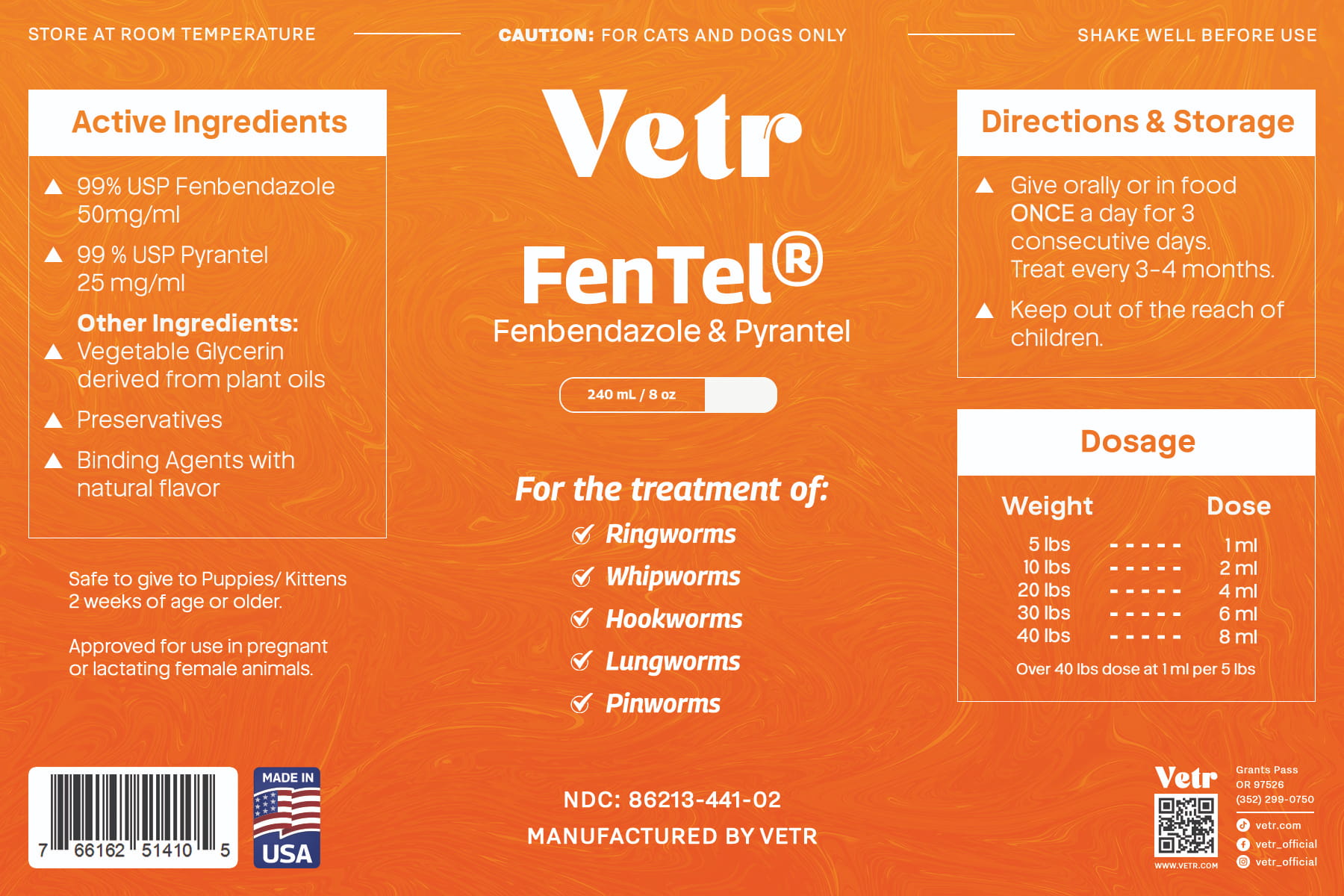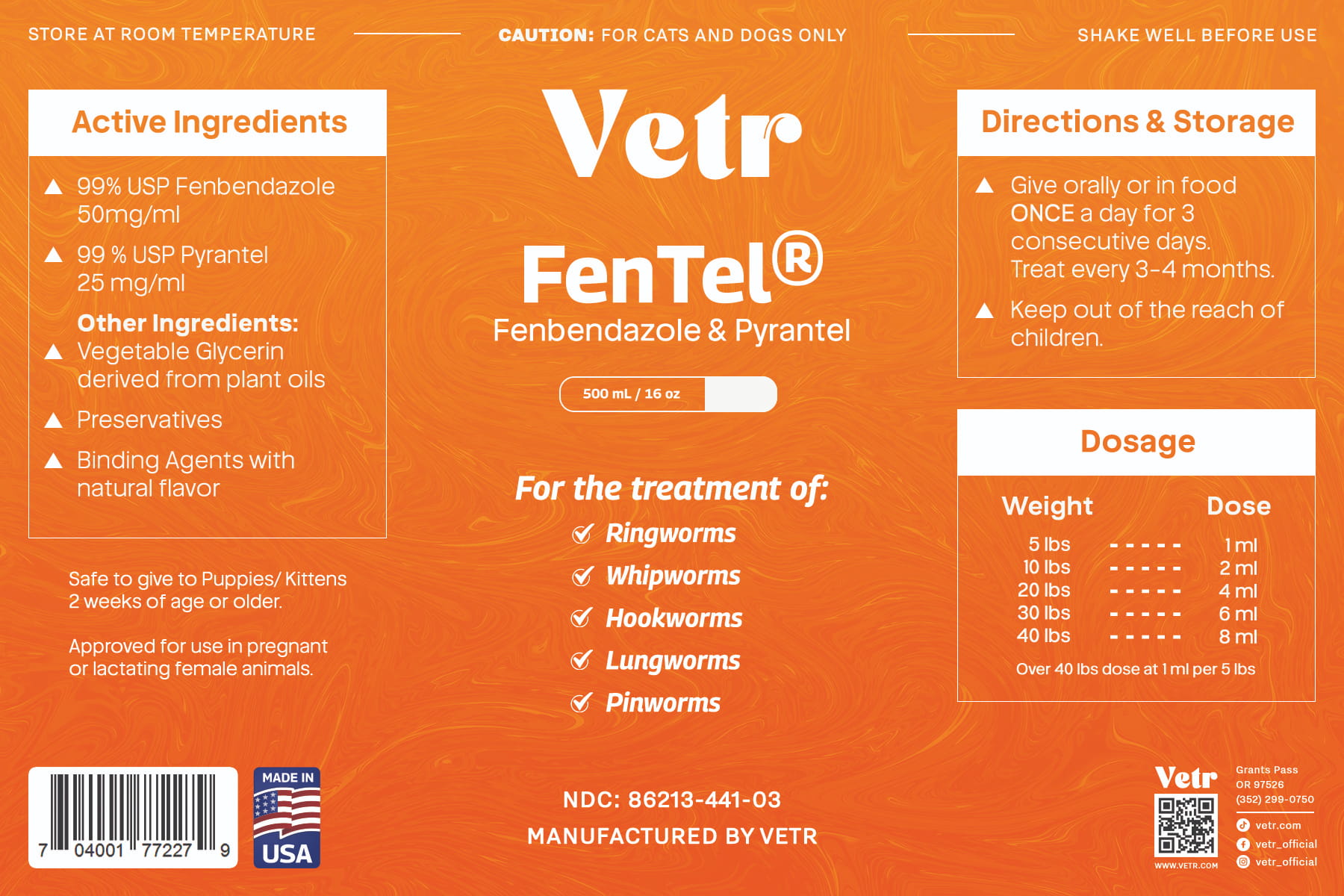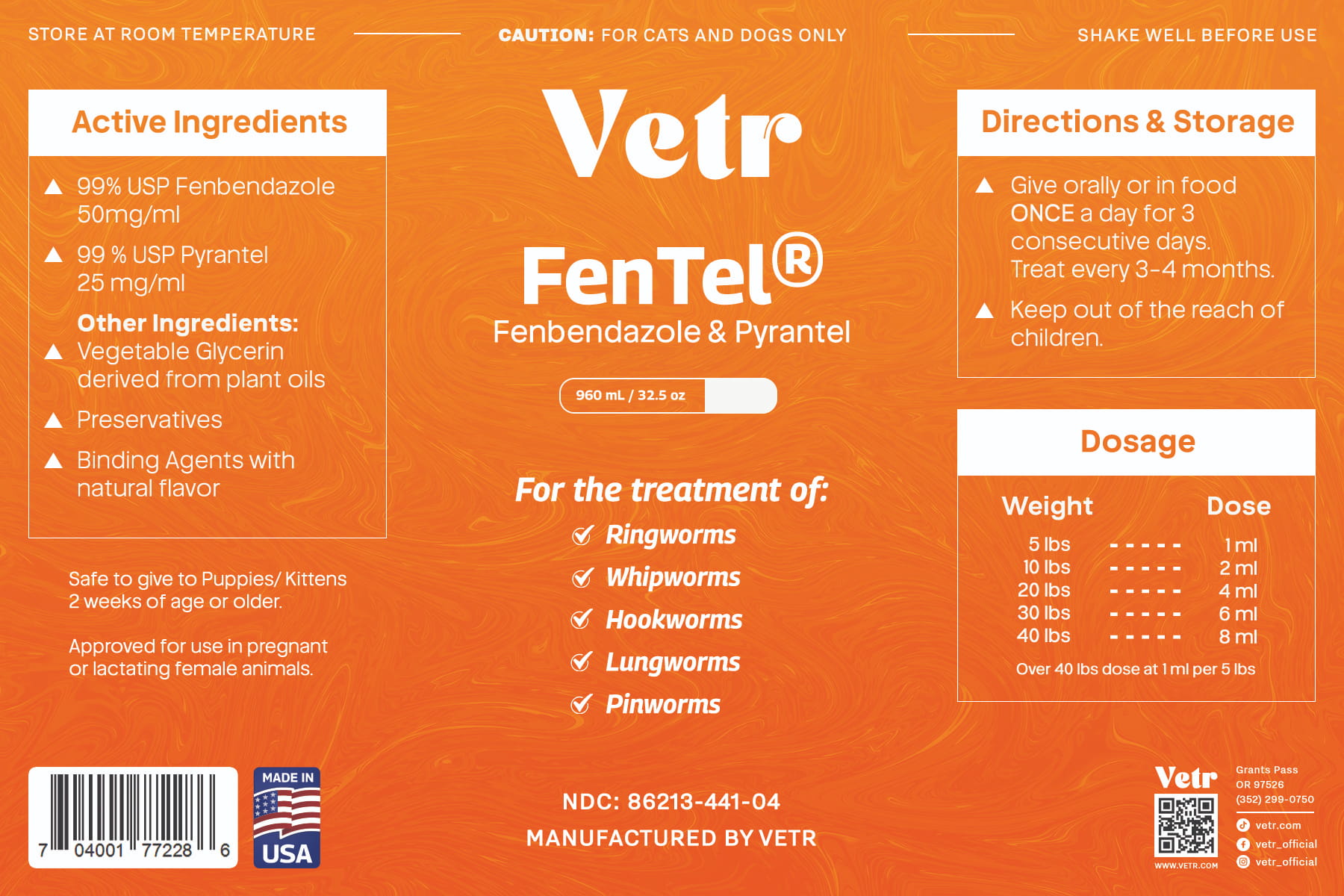 DRUG LABEL: FenTel
NDC: 86213-441 | Form: SUSPENSION
Manufacturer: Vetr LLC
Category: animal | Type: OTC ANIMAL DRUG LABEL
Date: 20260217

ACTIVE INGREDIENTS: FENBENDAZOLE 50 mg/1 mL; PYRANTEL PAMOATE 25 mg/1 mL
INACTIVE INGREDIENTS: GLYCERIN; POTASSIUM SORBATE; METHYLPARABEN; PROPYLPARABEN

Vetr FenTel (5% fenbendazole, 2.5% pyrantel suspension)

Caution

Do not administer to puppies and kittens under 2 weeks of age. May be given to pregnant or lactating females. KEEP OUT OF REACH OF CHILDREN.

Directions for Use

Shake well before use. Give 1 mL per 5 lbs body weight. Administer orally, or in food once per day for 3 consecutive days.

DOSAGE CHART:

Up to 5 lbs: 1 mL

10 lbs: 2 mL

20 lbs: 4 mL

30 lbs: 6 mL

40 lbs: 8 mL

*over 40 lbs, dose at 1 mL per 5 lbs body weight

Storage

Store at room temperature, at or below 25 C (<77 F)

Active Ingredients

fenbendazole USP, 50 mg/mL (5% w/v); pyrantel USP 25 mg/mL (2.5% w/v)

Other Ingredients

Certified vegetable glycerine, natural preservative, stabilizers and flavoring

Say goodby to worms. fenbendazole and pyrantel, in combination have been shown to be effective against Roundworms, Whipworms, Hookworms, Lungworms and Pinworms, and swell tolerated in dogs and cats.